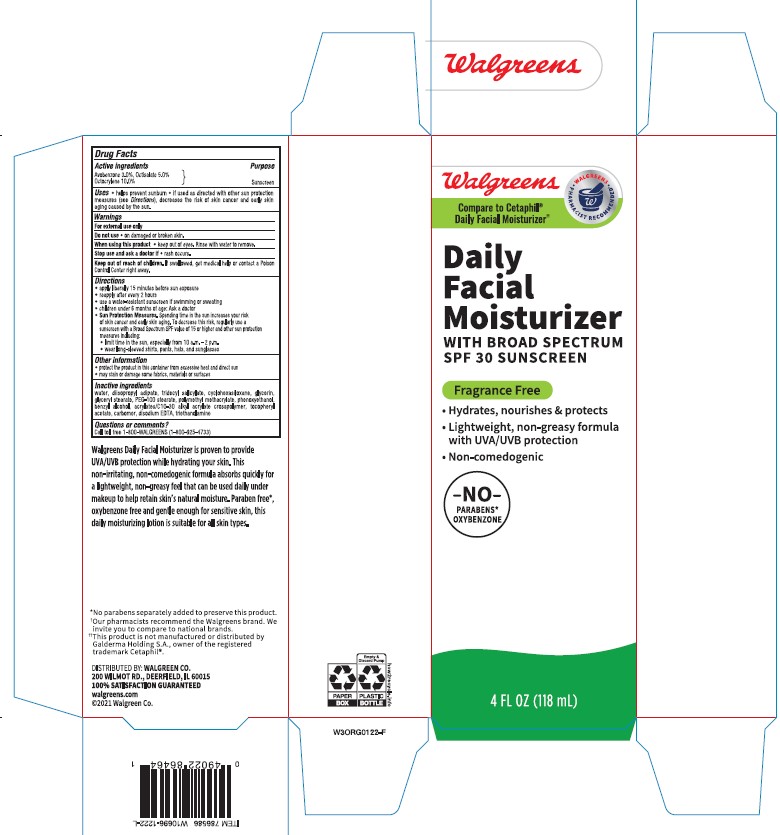 DRUG LABEL: Walgreens Daily Facial Moisturizer with Broad Spectrum SPF 30 Sunscreen
NDC: 0363-0172 | Form: LOTION
Manufacturer: WALGREEN COMPANY
Category: otc | Type: HUMAN OTC DRUG LABEL
Date: 20241011

ACTIVE INGREDIENTS: AVOBENZONE 30 mg/1 mL; OCTISALATE 50 mg/1 mL; OCTOCRYLENE 100 mg/1 mL
INACTIVE INGREDIENTS: CARBOMER COPOLYMER TYPE B (ALLYL PENTAERYTHRITOL CROSSLINKED); WATER; GLYCERIN; EDETATE DISODIUM; POLY(METHYL METHACRYLATE; 450000 MW); PHENOXYETHANOL; TRIDECYL SALICYLATE; PEG-100 STEARATE; CARBOMER INTERPOLYMER TYPE A (ALLYL SUCROSE CROSSLINKED); ETHYLHEXYLGLYCERIN; GLYCERYL 1-STEARATE; TROLAMINE; BENZYL ALCOHOL; DIISOPROPYL ADIPATE; .ALPHA.-TOCOPHEROL ACETATE; CYCLOMETHICONE 6

Walgreens Daily Facial Moisturizer with Broad Spectrum SPF 30 Sunscreen

Active ingredients

Avobenzone 3.0%, Octisalate 5.0%, Octocrylene 10.0%

Purpose

Sunscreen

Uses

- helps prevent sunburn
- if used as directed with other sun protection measures (see Directions), decreases the risk of skin cancer and early skin aging caused by the sun

Warnings

For external use only

Do not use

• on damaged or broken skin.

When using this product

• keep out of eyes. Rinse with water to remove.

Stop use and ask a doctor if

• rash occurs.

Keep out of reach of children.

If swallowed, get medical help or contact a Poison Control Center right away.

Directions

- apply liberally 15 minutes before sun exposure
- use a water resistant sunscreen if swimming or sweating
- reapply at least every 2 hours
- children under 6 months of age: Ask a doctor
- Sun Protection Measures. Spending time in the sun increases your risk of skin cancer and early skin aging. To decrease this risk, regularly use a sunscreen with a Broad Spectrum SPF value of 15 or higher and other sun protection measures including:

• limit time in the sun, especially from 10 a.m. - 2 p.m.

• wear long-sleeved shirts, pants, hats, and sunglasses

Other information

- protect the product in this container from excessive heat and direct sun
- may stain or damage some fabrics, materials or surfaces

Inactive ingredients

WATER, DIISOPROPYL ADIPATE, TRIDECYL SALICYLATE, CYCLOHEXASILOXANE, GLYCERIN, GLYCERYL STEARATE, PEG-100 STEARATE, POLYMETHYL METHACRYLATE, PHENOXYETHANOL, BENZYL ALCOHOL, ACRYLATES/C10-30 ALKYL ACRYLATE CROSSPOLYMER, TOCOPHERYL ACETATE, CARBOMER, DISODIUM EDTA, TRIETHANOLAMINE